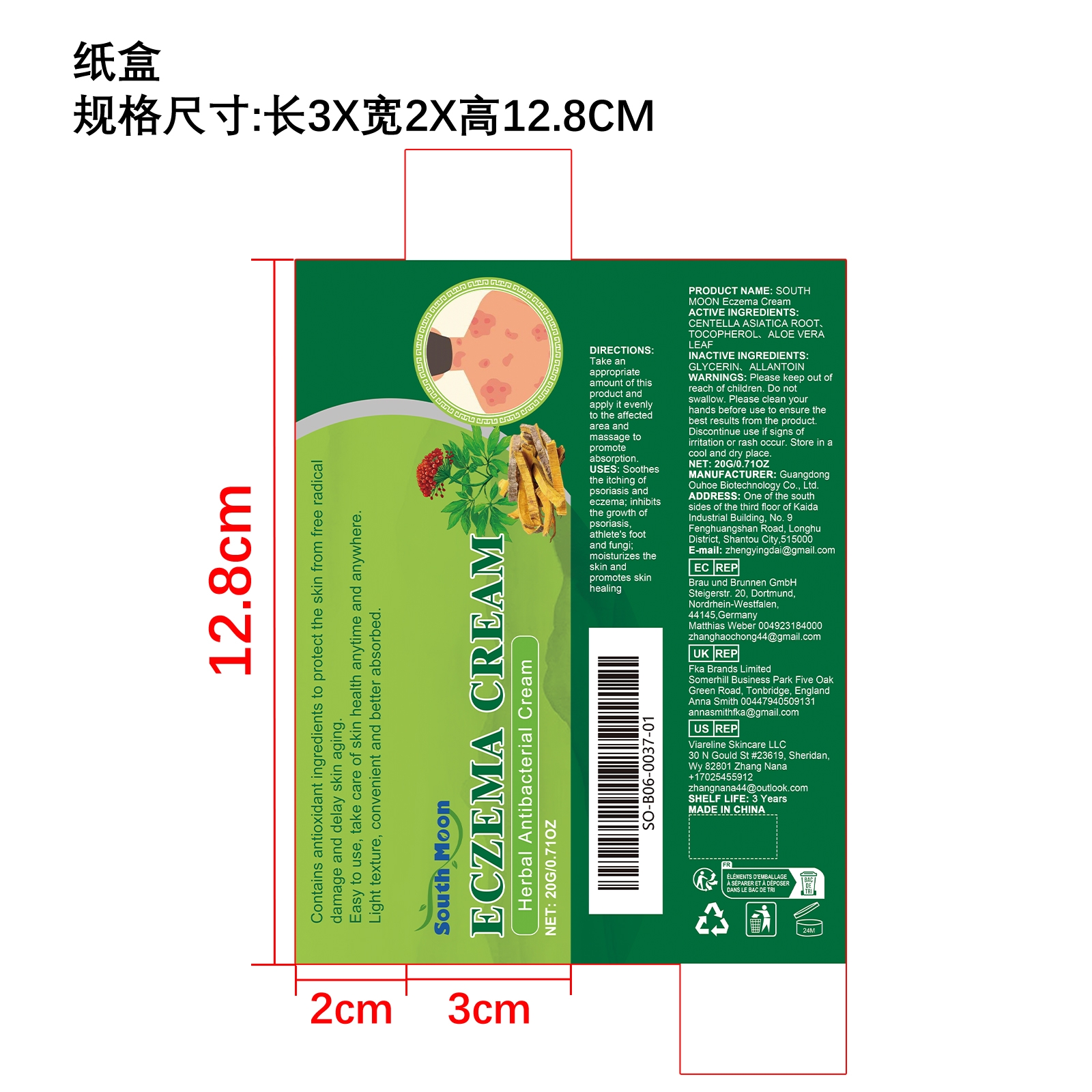 DRUG LABEL: SOUTH MOON Eczema Cream
NDC: 84744-062 | Form: CREAM
Manufacturer: Guangdong Ouhoe Biotechnology Co., Ltd.
Category: otc | Type: HUMAN OTC DRUG LABEL
Date: 20241024

ACTIVE INGREDIENTS: TOCOPHEROL 2 g/20 g; CENTELLA ASIATICA ROOT 6 g/20 g; ALOE VERA LEAF 3 g/20 g
INACTIVE INGREDIENTS: GLYCERIN 3 g/20 g; ALLANTOIN 6 g/20 g

ACTIVE INGREDIENTS

CENTELLA ASIATICA ROOT、TOCOPHEROL、ALOE VERA LEAF

purpose

Soothesthe itching of psoriasis and eczema; inhibits the growth of psoriasis, athlete's foot and fungi; moisturizes the skin and promotes skin healing

use

Take an appropriate amount of this product and apply it evenly to the affected area and massage to promote absorption.

WARNINGS

Please keep out of reach of children. Do not swallow. Please clean your hands before use to ensure the best results from the product. Discontinue use if signs of irritation or rash occur. Store in a cool and dry place.

KEEP OUT OF REACH OF CHILDREN

Please keep out of reach of children. Do not swallow.

STOP USE

Discontinue use if signs of irritation or rash occur.

stop use

Discontinue use if signs of irritation or rash occur.

STORAGE AND HANDLING

Store in a cool and dry place.

INACTIVE INGREDIENT

GLYCERIN、ALLANTOIN